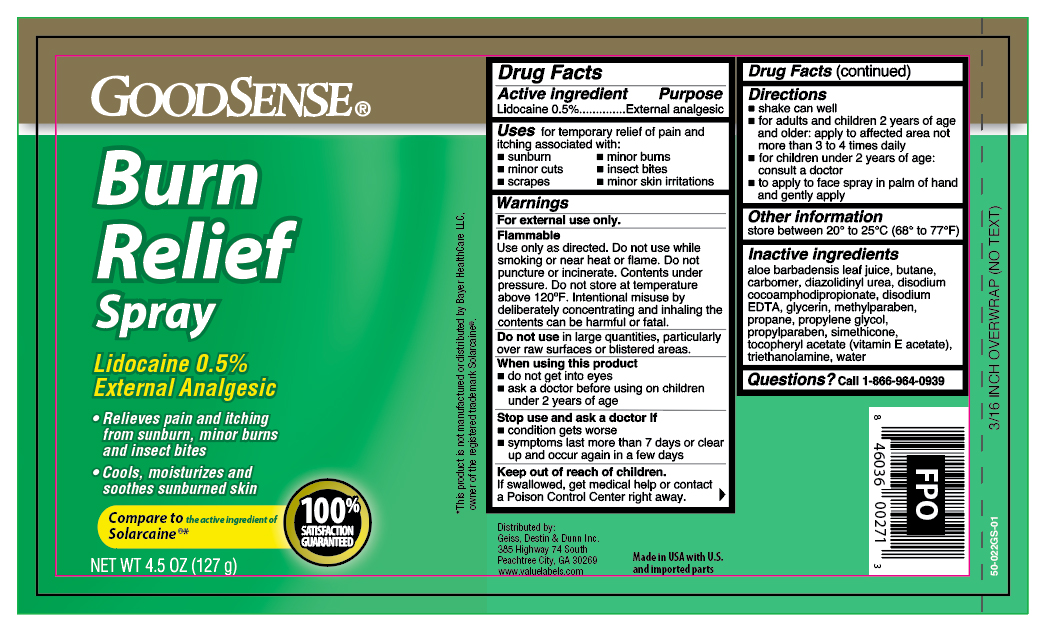 DRUG LABEL: Lidocaine
NDC: 50804-756 | Form: AEROSOL, SPRAY
Manufacturer: Perrigo Direct
Category: otc | Type: HUMAN OTC DRUG LABEL
Date: 20251030

ACTIVE INGREDIENTS: LIDOCAINE 0.64 g/127 g
INACTIVE INGREDIENTS: ALOE VERA LEAF; BUTANE; CARBOMER 934; DIAZOLIDINYL UREA; DISODIUM COCOAMPHODIPROPIONATE; EDETATE DISODIUM; GLYCERIN; METHYLPARABEN; PROPANE; PROPYLENE GLYCOL; PROPYLPARABEN; .ALPHA.-TOCOPHEROL ACETATE; TROLAMINE; WATER

Good Sense Burn Relief Spray

Active Ingredients

Lidocaine 0.5%

Purpose

External analgesic

Uses

for the temporary relief of pain and itching associated with:

- sunburn
- minor burns
- minor cuts
- scrapes
- insect bites
- minor skin irritations

Warnings

For external use only.

Flammable:

Do not use while smoking or near heat or flame. Do not puncture or incinerate. Contents under pressure. Do not store at temperature above 120ºF

Do not use

in large quantities, particularly over raw surfaces or blistered areas.

When using this product

- do not get into eyes
- ask a doctor before using on children under 2 years of age

Stop use and ask a doctor if

- condition gets worse
- symptoms last more than 7 days or clears up and occurs again in a few days

Keep out of reach of children.

If swallowed, get medical help or contact a Poison Control Center right away.

Directions

- shake can well
- for adults and children 2 years and older, apply to affected area not more than 3 to 4 times daily
- for children under 2 years of age, ask a doctor
- to apply to face spray in palm of hand and gently apply

Other information

store between 20º and 25ºC (68º and 77ºF)

Inactive ingredients

aloe barbadensis gel, butane, carbomer, diazolidinyl urea, disodium cocoamphodipropionate, disodium EDTA, glycerine, methylparaben, propane, propylene glycol, propylparaben, tocopheryl acetate (vitamin E acetate), triethanolamine, simethicone, water

Questions?

Call 1-888-423-0139

Principal Display Panel

GOODSENSE

Burn

Relief

Spray

Lidocaine 0.5%

External Analgesic

- Relieves pain and itching from sunburn, minor burns and insect bites
- Cools, moisturizes and soothes sunburned skin

Net WT 4.5 OZ (127g)